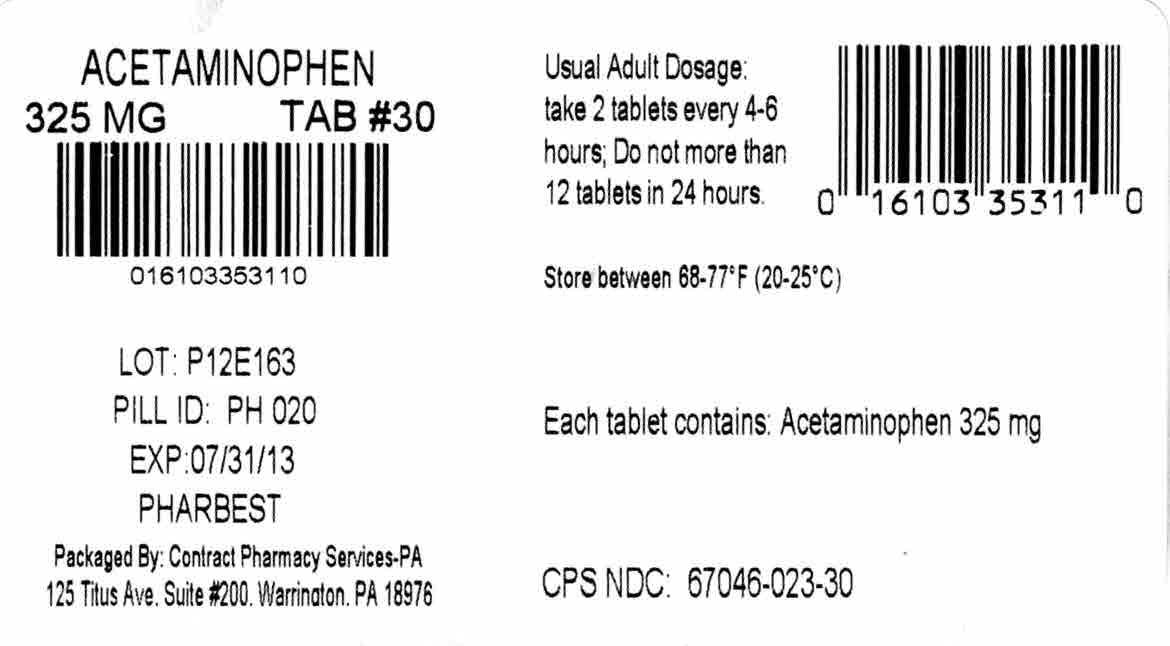 DRUG LABEL: Pharbetol
NDC: 67046-023 | Form: TABLET
Manufacturer: Coupler Enterprises
Category: otc | Type: HUMAN OTC DRUG LABEL
Date: 20210224

ACTIVE INGREDIENTS: ACETAMINOPHEN 325 mg/1 1
INACTIVE INGREDIENTS: POVIDONE; STARCH, CORN; SODIUM STARCH GLYCOLATE TYPE A CORN; STEARIC ACID

Acetaminophen 325 mg - Pharbest
Drug Facts

Active ingredient (per tablet)

Acetaminophen 325mg

Purpose

Pain reliever/Fever reducer

Uses

- Temporarily relieves minor aches and pains due to
-
  - the common cold
  - headache
  - backache
  - minor pain of arthritis
  - toothache
  - muscular aches
  - menstrual cramps
- Temporarily reduces fever

Warnings

Liver warning:This product contains acetaminophen. Severe liver damage may occur if

- Adult takes more than 12 tablets in 24 hours, which is the maximum daily amount
- Child takes more than 5 doses in 24 hours
- Taken with other drugs containing acetaminophen
- Adult has 3 or more alcoholic drinks every day while using this product

Do not use

- With any other drug containing acetaminophen (prescription or nonprescription). If you are not sure whether a drug contains acetaminophen, ask a doctor or pharmacist
- if you are allergic to acetaminophen or any of the inactive ingredients in this product

Ask a doctor before use if you have

liver disease.

Ask a doctor or pharmacist before use if you are

taking the blood thinning drug warfarin.

Stop use and ask a doctor if

- Pain gets worse or lasts more than 10 days in adults and children
- Pain gets worse or lasts more than 5 days in children under 12 years
- Fever gets worse or lasts more than 3 days
- New symptoms occur
- Redness or swelling is present

These could be sign of a serious condition.

If pregnant or breast-feeding,

ask a health professional before use.

Overdose warning:

Taking more than the recommended dose (overdose) may cause liver damage. In the case of accidental overdose, get medical help or contact a Poison Control Center right away.

Directions

- do not take more than directed (see overdose warning).

Adults and children 12 years and over | Take 2 tablets every 4 to 6 while symptoms last. Do not take more than 12 tablets in 24 hours.
Children 6 to under 12 years | Take 1 tablet every 4 to 6 while symptoms last. Do not take more than 5 tablets in 24 hours.
Children under 6 years | Do not use adult regular strength products in childern under 6 years of age; this will provide more than the recommended dose (overdose) and may cause liver damage.

Other information

- Tamper Evident: do not use if imprinted safety seal under cap is broken or missing
- store between 20-25°C (68-77°F)
- use by expiration date on package

Inactive ingredients:

Povidone, pregelatinized starch, sodium starch glycolate, stearic acid.

Questions?

Adverse drug event call: (866) 562-2756